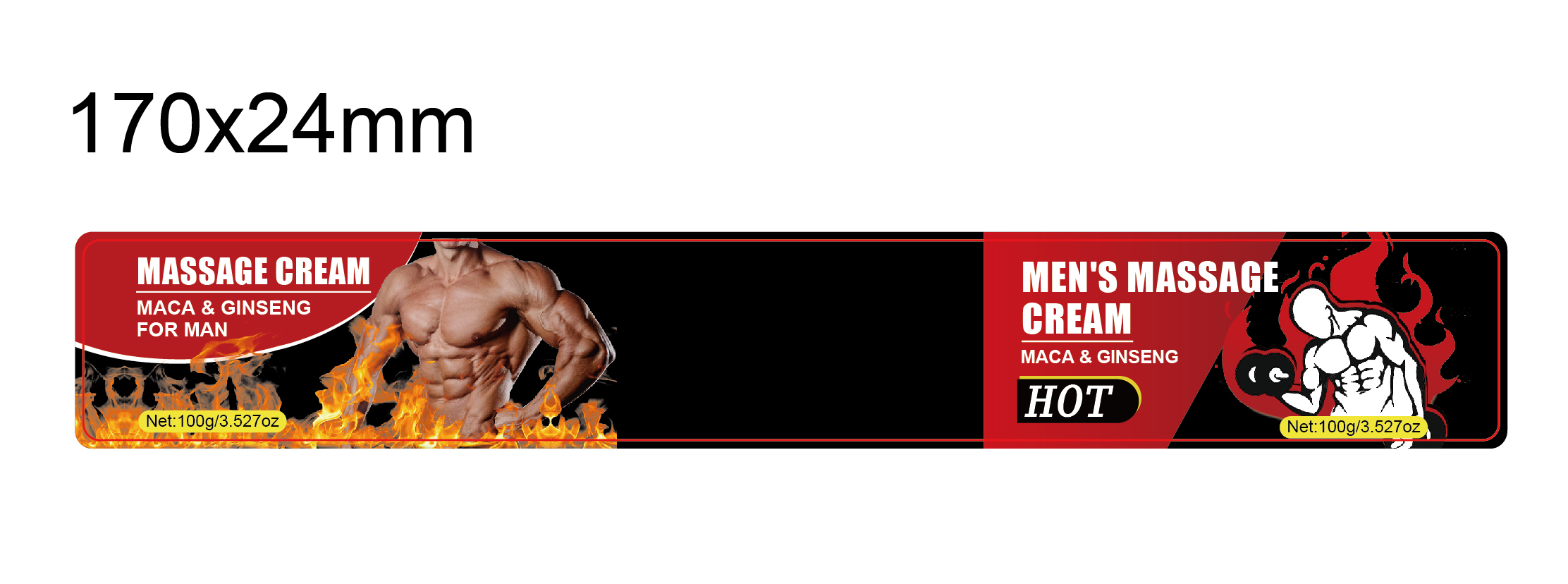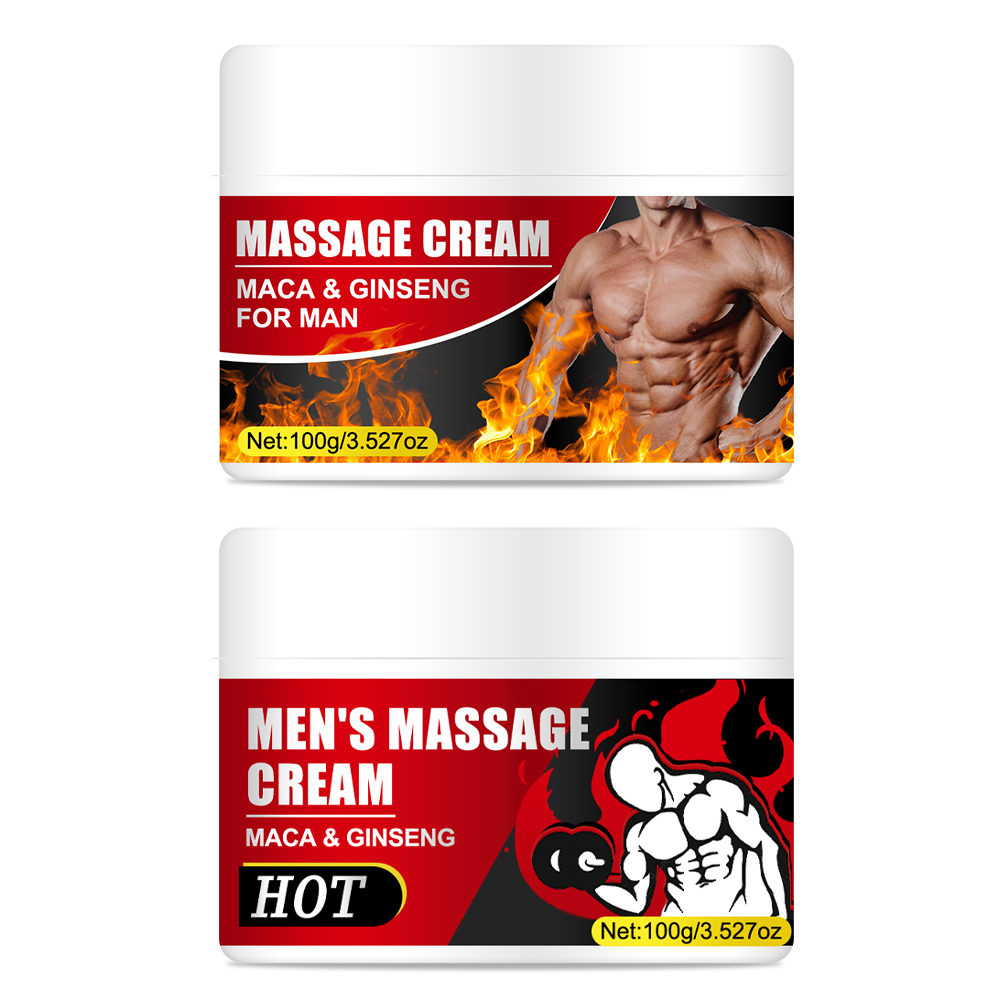 DRUG LABEL: Mens Massage Cream
NDC: 84025-244 | Form: CREAM
Manufacturer: Guangzhou Yanxi Biotechnology Co., Ltd
Category: otc | Type: HUMAN OTC DRUG LABEL
Date: 20241104

ACTIVE INGREDIENTS: GLYCERIN 3 mg/100 g; ALOE BARBADENSIS LEAF EXTRACT 5 mg/100 g
INACTIVE INGREDIENTS: WATER

DOSAGE AND ADMINISTRATION

Clean The Private Parts, Squeeze Out The Right Amount Of Cream And Smear The Required Parts.

WARNINGS

keep out of children

INACTIVE INGREDIENT

Aqua

INDICATIONS AND USAGE

for bady care

keep out of children

PURPOSE

Men’s energy strength massage spary god of war seven times a night.